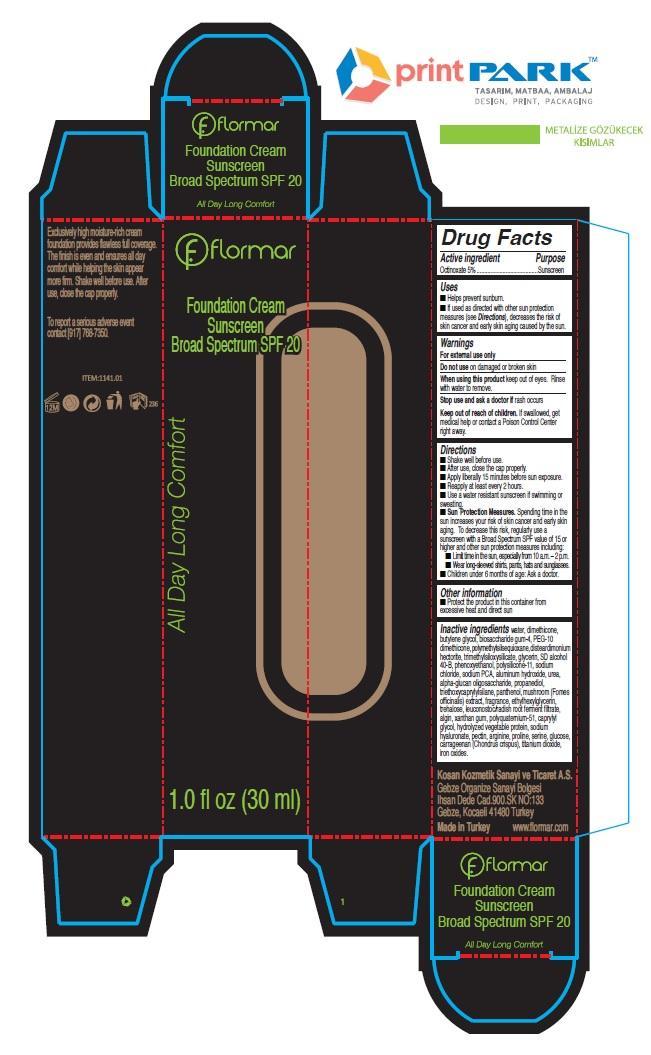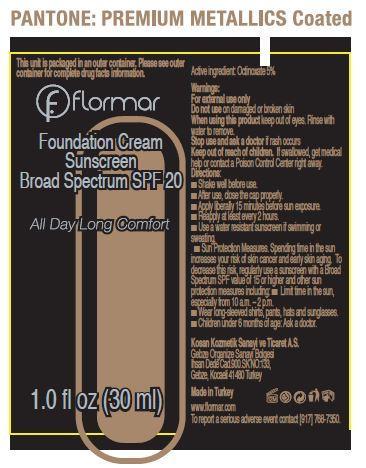 DRUG LABEL: flormar Foundation Sunscreen Broad Spectrum SPF 20 LF22 PURE BEIGE
NDC: 61722-067 | Form: CREAM
Manufacturer: Kosan Kozmetik Sanayi ve Ticaret A.S.
Category: otc | Type: HUMAN OTC DRUG LABEL
Date: 20191018

ACTIVE INGREDIENTS: OCTINOXATE 50 mg/1 mL
INACTIVE INGREDIENTS: WATER; DIMETHICONE; BUTYLENE GLYCOL; DISTEARDIMONIUM HECTORITE; GLYCERIN; PHENOXYETHANOL; SODIUM CHLORIDE; SODIUM PYRROLIDONE CARBOXYLATE; ALUMINUM HYDROXIDE; UREA; .ALPHA.-GLUCAN OLIGOSACCHARIDE; PROPANEDIOL; TRIETHOXYCAPRYLYLSILANE; PANTHENOL; LARICIFOMES OFFICINALIS FRUITING BODY; ETHYLHEXYLGLYCERIN; TREHALOSE; LEUCONOSTOC/RADISH ROOT FERMENT FILTRATE; SODIUM ALGINATE; XANTHAN GUM; CAPRYLYL GLYCOL; HYALURONATE SODIUM; PECTIN; ARGININE; PROLINE; SERINE; DEXTROSE; CARRAGEENAN; CHONDRUS CRISPUS; TITANIUM DIOXIDE; FERRIC OXIDE RED

flormar Foundation Cream Sunscreen Broad Spectrum SPF 20 LF22 PURE BEIGE

Active ingredient

Octinoxate 5%

Purpose

Sunscreen

Uses

- Helps prevent sunburn.
- If used as directed with other sun protection measures (see Directions), decreases the risk of skin cancer and early skin aging caused by the sun.

Warnings

For external use only

Do not use

on damaged or broken skin

When using this product

keep out of eyes. Rinse with water to remove.

Stop use and ask a doctor if

rash occurs

Keep out of reach of children.

If swallowed, get medical help or contact a Poison Control Center right away.

Directions

- Shake well before use.
- After use, close the cap properly.
- Apply liberally 15 minutes before sun exposure.
- Reapply at least every 2 hours.
- Use a water resistant sunscreen if swimming or sweating.
- Sun Protection Measures. Spending time in the sun increases your risk of skin cancer and early skin aging. To decrease this risk, regularly use a sunscreen with a Broad Spectrum SPF value of 15 or higher and other sun protection measures including:
- Limit time in the sun, especially from 10 a.m. – 2 p.m.
- Wear long-sleeved shirts, pants, hats and sunglasses.
- Children under 6 months of age: Ask a doctor.

Other information

- Protect the product in this container from excessive heat and direct sun

Inactive ingredients

water, dimethicone, butylene glycol, biosaccharide gum-4, PEG-10 dimethicone, polymethylsilsequioxane, disteardimonium hectorite, trimethylsiloxysilicate, glycerin, SD alcohol 40-B, phenoxyethanol, polysilicone-11, sodium chloride, sodium PCA, aluminum hydroxide, urea, alpha-glucan oligosaccharide, propanediol, triethoxycaprylylsilane, panthenol, mushroom (Fomes officinalis) extract, fragrance, ethylhexylglycerin, trehalose, leuconostoc/radish root ferment filtrate, algin, xanthan gum, polyquaternium-51, caprylyl glycol, hydrolyzed vegetable protein, sodium hyaluronate, pectin, arginine, proline, serine, glucose, carrageenan (Chondrus crispus), titanium dioxide, iron oxides.